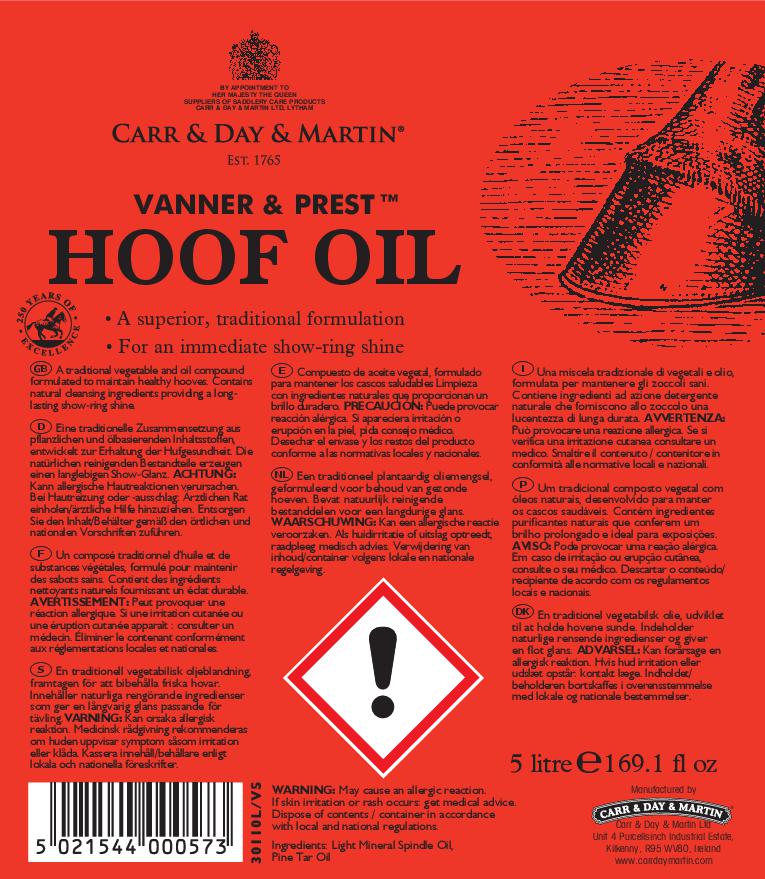 DRUG LABEL: Vanner and Prest Hoof
NDC: 43258-301 | Form: OIL
Manufacturer: Carr & Day & Martin Unlimited Company
Category: animal | Type: OTC ANIMAL DRUG LABEL
Date: 20241220

ACTIVE INGREDIENTS: WHITE PINE OIL 97 g/1 L
INACTIVE INGREDIENTS: PINE TAR

VANNER AND PREST HOOF OIL

WARNINGS

WARNING: May cause an allergic reaction. If skin irritation or rash occurs get medical advice. Dispose of contents / container in accordance with local and national regulations.

INDICATIONS AND USAGE

A traditional vegetable and oil compound formulated to maintain healthy hooves.

Contains natural cleansing ingredients providing a long-lasting show-ring shine.

Manufactured by

Carr & Day & Martin Ltd

Unit 4 Purcellsince Industrial Estate,

Kilkenny, R95 WV80, Ireland

www.carrdaymartin.com